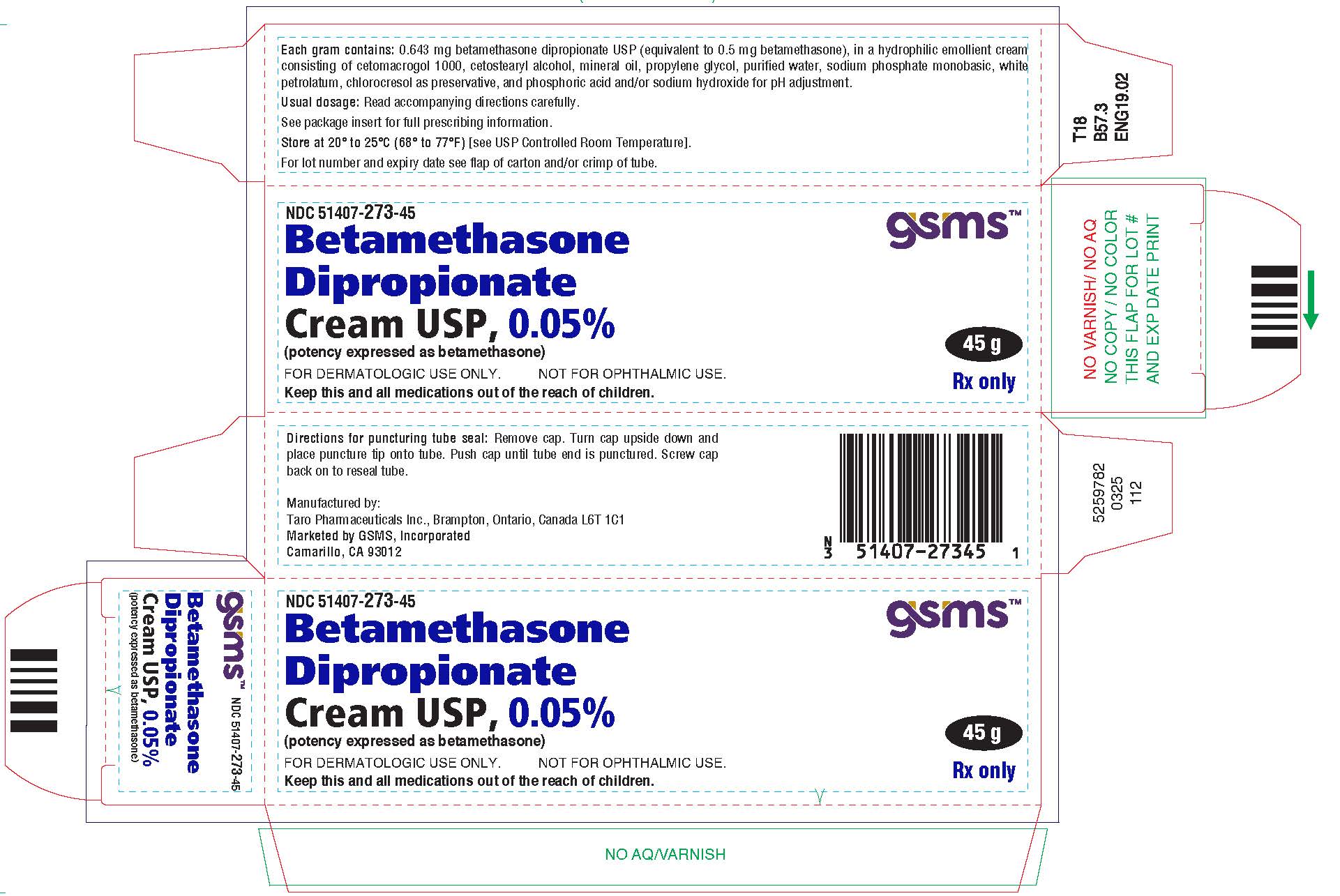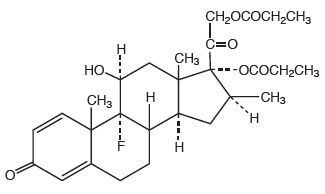 DRUG LABEL: Betamethasone Dipropionate
NDC: 51407-273 | Form: CREAM
Manufacturer: Golden State Medical Supply, Inc.
Category: prescription | Type: HUMAN PRESCRIPTION DRUG LABEL
Date: 20250710

ACTIVE INGREDIENTS: BETAMETHASONE DIPROPIONATE 0.5 mg/1 g
INACTIVE INGREDIENTS: CETETH-20; CETOSTEARYL ALCOHOL; MINERAL OIL; PROPYLENE GLYCOL; WATER; SODIUM PHOSPHATE, MONOBASIC, UNSPECIFIED FORM; PETROLATUM; CHLOROCRESOL; PHOSPHORIC ACID; SODIUM HYDROXIDE

Betamethasone Dipropionate
Cream USP, 0.05%
(potency expressed as betamethasone)

FOR DERMATOLOGIC USE ONLY. NOT FOR OPHTHALMIC USE.

Rx only

DESCRIPTION

Betamethasone Dipropionate Cream USP, 0.05% contains betamethasone dipropionate, USP, a synthetic adrenocorticosteroid, for dermatologic use. Betamethasone, an analog of prednisolone, has a high degree of glucocorticoid activity and a slight mineralocorticoid activity.

Betamethasone dipropionate is the 17, 21-dipropionate ester of betamethasone.

Betamethasone dipropionate is a white to creamy white, odorless crystalline powder, insoluble in water.

Chemically, it is 9-Fluoro-11β,17,21-trihydroxy-16β-methylpregna-1,4-diene-3,20-dione 17,21-dipropionate. The structural formula is:

Each gram of Betamethasone Dipropionate Cream USP, 0.05% contains: 0.643 mg betamethasone dipropionate USP (equivalent to 0.5 mg betamethasone), in a hydrophilic emollient cream consisting of cetomacrogol 1000, cetostearyl alcohol, mineral oil, propylene glycol, purified water, sodium phosphate monobasic, white petrolatum, chlorocresol as preservative, and phosphoric acid and/or sodium hydroxide for pH adjustment.

CLINICAL PHARMACOLOGY

The corticosteroids are a class of compounds comprising steroid hormones, secreted by the adrenal cortex and their synthetic analogs. In pharmacologic doses corticosteroids are used primarily for their anti-inflammatory and/or immunosuppressive effects.

Topical corticosteroids, such as betamethasone dipropionate, are effective in the treatment of corticosteroid-responsive dermatoses primarily because of their anti-inflammatory, antipruritic, and vasoconstrictive actions. However, while the physiologic, pharmacologic, and clinical effects of the corticosteroids are well known, the exact mechanisms of their actions in each disease are uncertain. Betamethasone dipropionate, a corticosteroid, has been shown to have topical (dermatologic) and systemic pharmacologic and metabolic effects characteristic of this class of drugs.

Pharmacokinetics

The extent of percutaneous absorption of topical corticosteroids is determined by many factors including the vehicle, the integrity of the epidermal barrier, and the use of occlusive dressings. (See DOSAGE AND ADMINISTRATION).

Topical corticosteroids can be absorbed through normal intact skin. Inflammation and/or other disease processes in the skin increase percutaneous absorption. Occlusive dressings substantially increase the percutaneous absorption of topical corticosteroids (See DOSAGE AND ADMINISTRATION).

Once absorbed through the skin, topical corticosteroids are handled through pharmacokinetic pathways similar to systemically administered corticosteroids. Corticosteroids are bound to plasma proteins in varying degrees. Corticosteroids are metabolized primarily in the liver and are then excreted by the kidneys. Some of the topical corticosteroids and their metabolites are also excreted into the bile.

Sixty-three pediatric patients ages 1 to 12 years, with atopic dermatitis, were enrolled in an open-label, hypothalamic-pituitary-adrenal (HPA) axis safety study. Betamethasone dipropionate cream was applied twice daily for 2 to 3 weeks over a mean body surface area of 40% (range 35% to 90%). In 10 of 43 (23%) evaluable patients, adrenal suppression was indicated by either a ≤ 5 mcg/dL pre-stimulation cortisol, or a cosyntropin post-stimulation cortisol ≤ 18 mcg/dL and/or an increase of < 7 mcg/dL from the baseline cortisol. Studies performed with betamethasone dipropionate cream indicate that it is in the medium range of potency as compared with other topical corticosteroids.

INDICATIONS AND USAGE

Betamethasone dipropionate cream is a medium-potency corticosteroid indicated for relief of the inflammatory and pruritic manifestations of corticosteroid responsive dermatoses in patients 13 years and older.

CONTRAINDICATIONS

Betamethasone dipropionate cream is contraindicated in patients who are hypersensitive to betamethasone dipropionate, to other corticosteroids, or to any ingredient in this preparation.

PRECAUTIONS

General

Systemic absorption of topical corticosteroids has produced reversible hypothalamic-pituitary-adrenal (HPA) axis suppression, manifestations of Cushing's syndrome, hyperglycemia, and glucosuria in some patients.

Conditions which augment systemic absorption include the application of the more potent steroids, use over large surface areas, prolonged use, and the addition of occlusive dressings. Use of more than one corticosteriod-containing product at the same time may increase total systemic glucocorticoid exposure. (See DOSAGE AND ADMINISTRATION.)

Therefore, patients receiving a large dose of a potent topical steroid applied to a large surface area should be evaluated periodically for evidence of HPA axis suppression by using the urinary free cortisol and ACTH stimulation tests. If HPA axis suppression is noted, an attempt should be made to withdraw the drug, to reduce the frequency of application, or to substitute a less potent steroid.

Recovery of HPA axis function is generally prompt and complete upon discontinuation of the drug. In an open-label pediatric study of 43 evaluable patients, of the 10 subjects who showed evidence of suppression, 2 subjects were tested 2 weeks after discontinuation of betamethasone dipropionate cream, 0.05%, and 1 of the 2 (50%) had complete recovery of HPA axis function.

Infrequently, signs and symptoms of steroid withdrawal may occur, requiring supplemental systemic corticosteroids.

Pediatric patients may absorb proportionally larger amounts of topical corticosteroids and thus be more susceptible to systemic toxicity (See PRECAUTIONS - Pediatric Use). If irritation develops, topical corticosteroids should be discontinued and appropriate therapy instituted.

In the presence of dermatological infections, the use of an appropriate antifungal or antibacterial agent should be instituted. If a favorable response does not occur promptly, the corticosteroid should be discontinued until the infection has been adequately controlled.

Information for Patients

This information is intended to aid in the safe and effective use of this medication. It is not a disclosure of all possible adverse or intended effects.

Patients using topical corticosteroids should receive the following information and instructions:

1. This medication is to be used as directed by the physician. It is for external use only. Avoid contact with the eyes.
2. Patients should be advised not to use this medication for any disorder other than that for which it was prescribed.
3. The treated skin area should not be bandaged or otherwise covered or wrapped as to be occlusive. (See DOSAGE AND ADMINISTRATION.)
4. Patients should report any signs of local adverse reactions.
5. Other corticosteroid-containing products should not be used with betamethasone dipropionate cream without first talking to your physician.

Laboratory Tests

The following tests may be helpful in evaluating HPA axis suppression:

- Urinary free cortisol test
- ACTH stimulation test

Carcinogenesis, Mutagenesis, and Impairment of Fertility

Long-term animal studies have not been performed to evaluate the carcinogenic potential of betamethasone dipropionate.

Betamethasone was negative in the bacterial mutagenicity assay (Salmonella typhimuriumand Escherichia coli), and in the mammalian cell mutagenicity assay (CHO/HGPRT). It as positive in the in-vitrohuman lymphocyte chromosome aberration assay, and equivocal in the in-vivomouse bone marrow micronucleus assay. This pattern of response is similar to that of dexamethasone and hydrocortisone.

Reproductive studies with betamethasone dipropionate carried out in rabbits at doses of 1.0 mg/kg by the intramuscular route and in mice up to 33 mg/kg by the intramuscular route indicated no impairment of fertility except for dose-related increases in fetal resorption rates in both species. These doses are approximately 0.5 and 4 fold the estimated maximum human dose based on a mg/m^2comparison, respectively.

Pregnancy Category C

Corticosteroids are generally teratogenic in laboratory animals when administered systemically at relatively low dosage levels.

Betamethasone dipropionate has been shown to be teratogenic in rabbits when given by the intramuscular route at doses of 0.05 mg/kg. This dose is approximately 0.03 fold the estimated maximum human dose based on a mg/m^2comparison. The abnormalities observed included umbilical hernias, cephalocele and cleft palates.

Some corticosteroids have been shown to be teratogenic after dermal application in laboratory animals. There are no adequate and well-controlled studies in pregnant women on teratogenic effects from topically applied corticosteroids.

Therefore, topical corticosteroids should be used during pregnancy only if the potential benefit justifies the potential risk to the fetus. Drugs of this class should not be used extensively on pregnant patients, in large amounts, or for prolonged periods of time.

Nursing Mothers

It is not known whether topical administration of corticosteroids could result in sufficient systemic absorption to produce detectable quantities in breast milk. Systemically administered corticosteroids are secreted into breast milk in quantities not likely to have a deleterious effect on the infant. Nevertheless, caution should be exercised when topical corticosteroids are prescribed for a nursing woman.

Pediatric Use

Use of betamethasone dipropionate cream, 0.05%, in pediatric patients 12 years of age and younger is not recommended. (See CLINICAL PHARMACOLOGYand ADVERSE REACTIONS.)

In an open-label study, 10 of 43 (23%) evaluable pediatric patients (aged 2 years to 12 years old) using betamethasone dipropionate cream for treatment of atopic dermatitis for 2 to 3 weeks demonstrated HPA axis suppression. The proportion of patients with adrenal suppression in this study was progressively greater, the younger the age group. (See CLINICAL PHARMACOLOGY - Pharmacokinetics.)

Pediatric patients may demonstrate greater susceptibility to topical corticosteroid-induced HPA axis suppression and Cushing's syndrome than mature patients because of a larger skin surface area to body weight ratio.The study described above supports this premise, as suppression in 9 to 12 year olds, and 2 to 5 year olds was 14%, 23%, and 30%, respectively.

Hypothalamic-pituitary-adrenal (HPA) axis suppression, Cushing's syndrome, and intracranial hypertension have been reported in pediatric patients receiving topical corticosteroids. Manifestations of adrenal suppression in pediatric patients include linear growth retardation, delayed weight gain, low plasma cortisol levels, and absence of response to ACTH stimulation. Manifestations of intracranial hypertension include bulging fontanelles, headaches and bilateral papilledema.

Administration of topical corticosteroids to pediatric patients should be limited to the least amount compatible with an effective therapeutic regimen. Chronic corticosteroid therapy may interfere with the growth and development of pediatric patients.

ADVERSE REACTIONS

The following local adverse reactions are reported infrequently when betamethasone dipropionate cream USP, 0.05% is used as recommended in the DOSAGE AND ADMINISTRATIONsection. These reactions are listed in an approximate decreasing order of occurrence: burning, itching, irritation, dryness, folliculitis, hypertrichosis, acneiform eruptions, hypopigmentation, perioral dermatitis, allergic contact dermatitis, maceration of the skin, secondary infections, skin atrophy, striae and miliaria. Adverse reactions reported to be possibly or probably related to treatment with betamethasone dipropionate cream during a pedatric clinical study include signs of skin atrophy (brusing, shininess). Skin atrophy occurred in 3 of 63 (5%) patients, a 3-year old, a 5-year old, and a 7-year old.

Systemic absorption of topical corticosteroids has produced reversible hypothalamic-pituitary-adrenal (HPA) axis suppression, manifestations of Cushing's syndrome, hyperglycemia, and glucosuria in some patients.

OVERDOSAGE

Topically applied corticosteroids can be absorbed in sufficient amounts to produce systemic effects (See PRECAUTIONS).

DOSAGE AND ADMINISTRATION

Apply a thin film of betamethasone dipropionate cream USP, 0.05% to the affected skin areas once daily. In some cases, twice-daily dosage may be necessary.

Betamethasone dipropionate cream USP, 0.05% should not be used with occlusive dressings.

HOW SUPPLIED

Betamethasone Dipropionate Cream USP, 0.05% is supplied in 15 gram (NDC 51407-273-15) and 45 gram (NDC 51407-273-45) tubes.

STORAGE AND HANDLING

Store at 20° to 25°C (68° to 77°F)[see USP Controlled Room Temperature].

Mfd. by: Taro Pharmaceuticals Inc., Brampton, Ontario, Canada L6T 1C1
Dist. by: Taro Pharmaceuticals U.S.A., Inc., Hawthorne, NY 10532

Revised: June, 2016

PK-1193-5
0616-5
74

Marketed by:

GSMS, Inc.

Camarillo, CA 93012 USA

PRINCIPAL DISPLAY PANEL - 45 g Tube Carton

NDC 51407-273-45

45 g

Betamethasone
Dipropionate
Cream USP, 0.05%
(potency expressed as betamethasone)

FOR DERMATOLOGIC USE ONLY.
NOT FOR OPHTHALMIC USE.

Rx only

Keep this and all medications out of the reach of children.